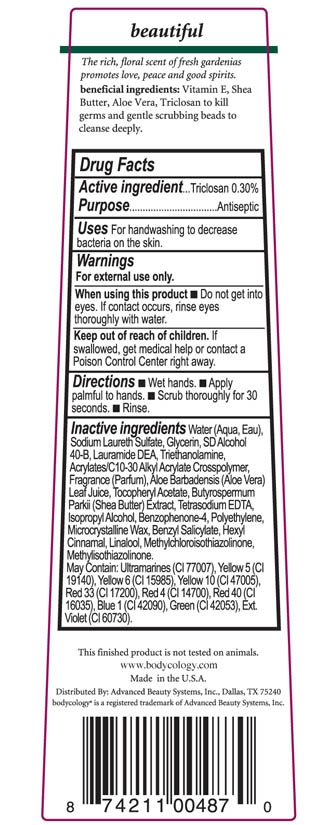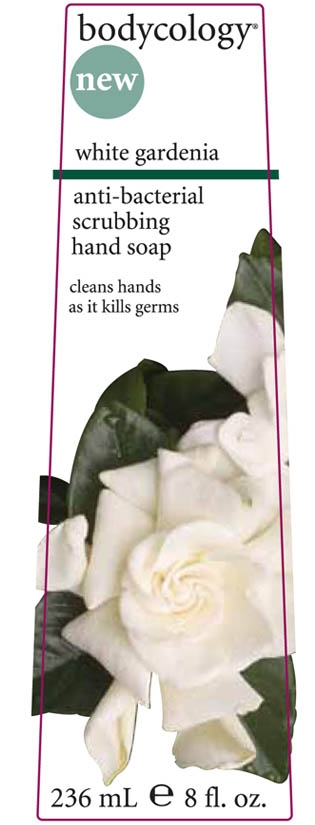 DRUG LABEL: Bodycology white gardenia anti-bacterial scrubbing hand soap
NDC: 65663-019 | Form: LIQUID
Manufacturer: American Blending and Filling
Category: otc | Type: HUMAN OTC DRUG LABEL
Date: 20100503

ACTIVE INGREDIENTS: Triclosan .30 mL/100 mL

Drug Facts

Active Ingredient

Triclosan

Purpose Antiseptic

Uses For handwashing to decrease bacteria on the skin.

Warnings For external use only

When using this product Do not get into eyes. If contact occurs, rinse eyes throughly with water.

Keep out of reach of children. If swallowed, get medical help or contact a Poison Control Center right away.

Directions Wet hands. Apply palmful to hands. Scrub thoroughly for 30 seconds. Rinse.

INACTIVE INGREDIENT

Inactive Ingredients Water (Aqua, Eau), Sodium Laureth Sulfate, Glycerine, SD Alcohol 40B, Lauramide DEA, Triethanolamine, Acrylates/C10-30 Alkyl Acrylate Crosspolymer, Fragrance (Parfum), Aloe Barbadensis (Aloe Vera) Leaf Juice, Tocopheryl Acetate, Butyrospermum Parkii (Shea Butter) Extract, Tetrasodium EDTA, Isopropyl Alcohol, Benzophenone-4, Polyethylene, Microcrystalline Wax, Benzyl Salicylate, Hexyl Cinnamal, Linalool, Methylchloroisothiazolinone, Methylisothaizolinone. May Contain: Ultramarines (Cl 77007), Yellow 5 (Cl 19140), Yellow 6 (CL 15985), Yellow 10 (Cl 47005), Red 33 (Cl 17200), Red 4 (Cl 14700), Red 40 (Cl 16035), Blue 1 (Cl 42090), Green (Cl 42053), Ext. Violet (Cl 60730).